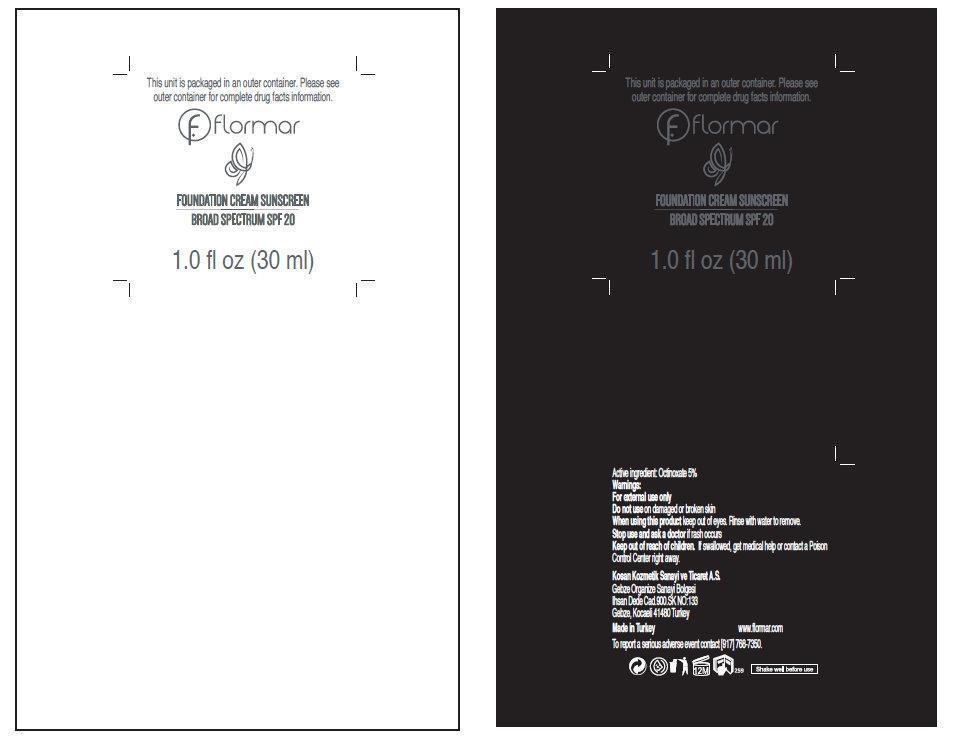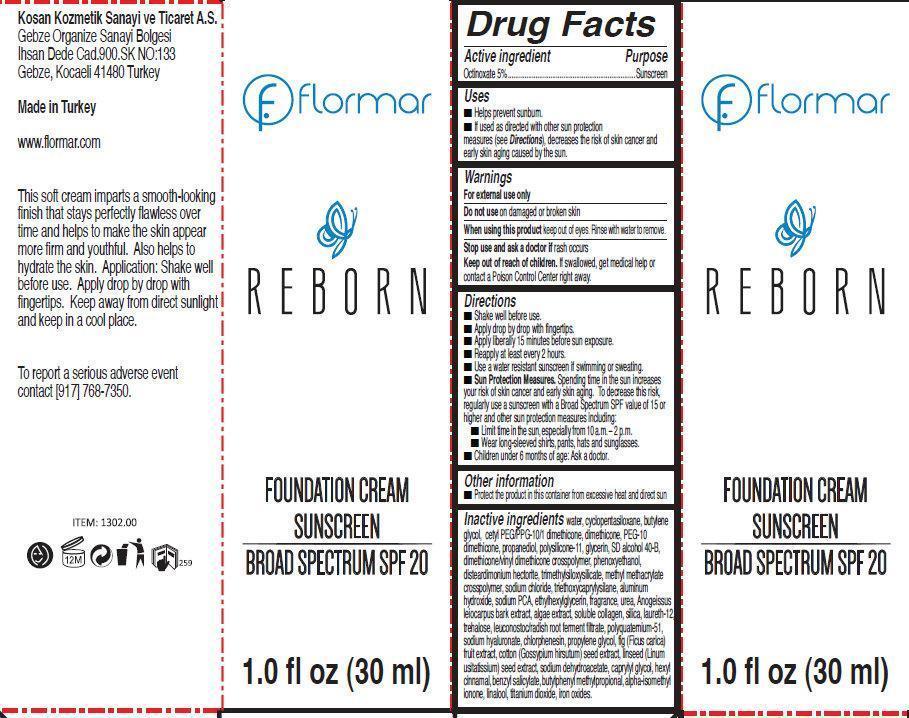 DRUG LABEL: flormar REBORN FOUNDATION SUNSCREEN BROAD SPECTRUM SPF 20 SF13 Nude Ivory
NDC: 61722-204 | Form: CREAM
Manufacturer: Kosan Kozmetik Sanayi ve Ticaret A.S.
Category: otc | Type: HUMAN OTC DRUG LABEL
Date: 20191018

ACTIVE INGREDIENTS: OCTINOXATE 50 mg/1 mL
INACTIVE INGREDIENTS: WATER; CYCLOMETHICONE 5; BUTYLENE GLYCOL; DIMETHICONE; PROPANEDIOL; GLYCERIN; PHENOXYETHANOL; DISTEARDIMONIUM HECTORITE; SODIUM CHLORIDE; TRIETHOXYCAPRYLYLSILANE; ALUMINUM HYDROXIDE; SODIUM PYRROLIDONE CARBOXYLATE; ETHYLHEXYLGLYCERIN; UREA; ANOGEISSUS LEIOCARPUS BARK; SILICON DIOXIDE; LAURETH-12; TREHALOSE; LEUCONOSTOC/RADISH ROOT FERMENT FILTRATE; HYALURONATE SODIUM; CHLORPHENESIN; PROPYLENE GLYCOL; COTTON SEED; FLAX SEED; SODIUM DEHYDROACETATE; CAPRYLYL GLYCOL; .ALPHA.-HEXYLCINNAMALDEHYDE; BENZYL SALICYLATE; BUTYLPHENYL METHYLPROPIONAL; ISOMETHYL-.ALPHA.-IONONE; LINALOOL, (+/-)-; TITANIUM DIOXIDE; FERRIC OXIDE RED

flormar REBORN FOUNDATION CREAM SUNSCREEN BROAD SPECTRUM SPF 20 SF13 Nude Ivory

Active ingredient

Octinoxate 5%

Purpose

Sunscreen

Uses

- Helps prevent sunburn.
- If used as directed with other sun protection measures (see Directions), decreases the risk of skin cancer and early skin aging caused by the sun.

Warnings

For external use only

Do not use

on damaged or broken skin

When using this product

keep out of eyes. Rinse with water to remove.

Stop use and ask a doctor if

rash occurs

Keep out of reach of children.

If swallowed, get medical help or contact a Poison Control Center right away.

Directions

- Shake well before use.
- Apply drop by drop with fingertips.
- Apply liberally 15 minutes before sun exposure.
- Reapply at least every 2 hours.
- Use a water resistant sunscreen if swimming or sweating.
- Sun Protection Measures. Spending time in the sun increases your risk of skin cancer and early skin aging. To decrease this risk, regularly use a sunscreen with a Broad Spectrum SPF value of 15 or higher and other sun protection measures including:
-
  - Limit time in the sun, especially from 10 a.m. – 2 p.m.
  - Wear long-sleeved shirts, pants, hats and sunglasses.
- Children under 6 months of age: Ask a doctor.

Other information

- Protect the product in this container from excessive heat and direct sun

Inactive ingredients

water, cyclopentasiloxane, butylene glycol, cetyl PEG/PPG-10/1 dimethicone, dimethicone, PEG-10 dimethicone, propanediol, polysilicone-11, glycerin, SD alcohol 40-B, dimethicone/vinyl dimethicone crosspolymer, phenoxyethanol, disteardimonium hectorite, trimethylsiloxysilicate, methyl methacrylate crosspolymer, sodium chloride, triethoxycaprylysilane, aluminum hydroxide, sodium PCA, ethylhexylglycerin, fragrance, urea, Anogeissus leiocarpus bark extract, algae extract, soluble collagen, silica, laureth-12, trehalose, leuconostoc/radish root ferment filtrate, polyquaternium-51, sodium hyaluronate, chlorphenesin, propylene glycol, fig (Ficus carica) fruit extract, cotton (Gossypium hirsutum) seed extract, linseed (Linumusitatissium) seed extract, sodium dehydroacetate, caprylyl glycol, hexyl cinnamal, benzyl salicylate, butylphenyl methylpropional, alpha-isomethylionone, linalool, titanium dioxide, iron oxides.